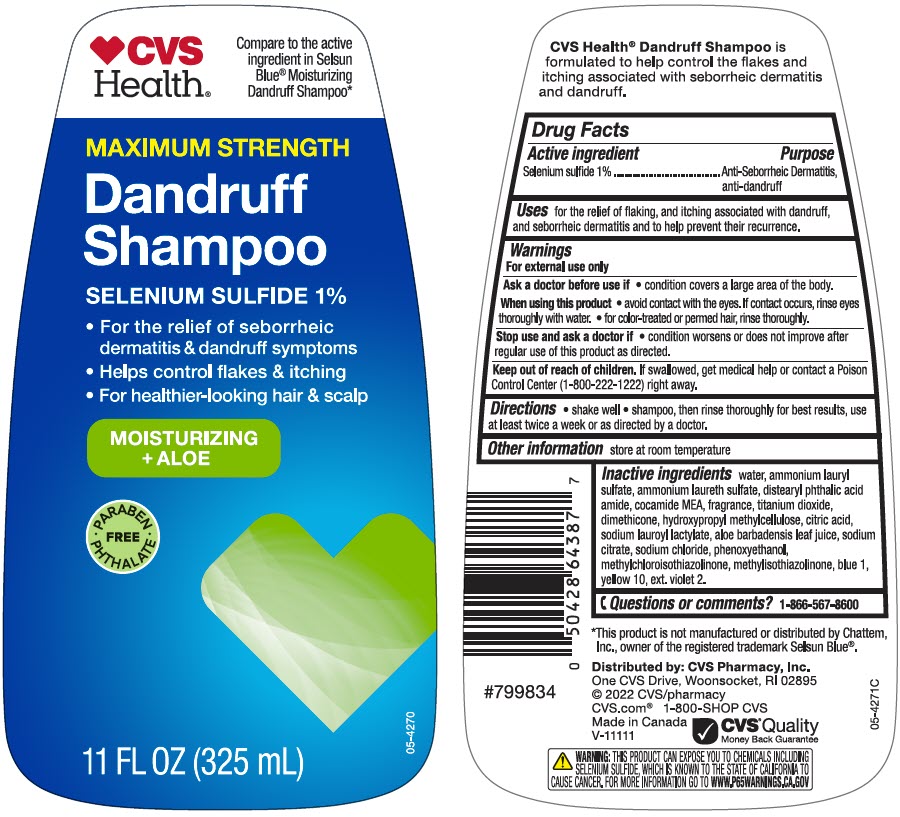 DRUG LABEL: CVS Health MAXIMUM STRENGTH Dandruff
NDC: 51316-387 | Form: SHAMPOO
Manufacturer: CVS Health
Category: otc | Type: HUMAN OTC DRUG LABEL
Date: 20240924

ACTIVE INGREDIENTS: Selenium sulfide 10 mg/1 mL
INACTIVE INGREDIENTS: Water; Ammonium Lauryl Sulfate; AMMONIUM LAURETH-5 SULFATE; DISTEARYL PHTHALAMIC ACID; COCO MONOETHANOLAMIDE; Titanium Dioxide; Dimethicone; HYPROMELLOSE, UNSPECIFIED; CITRIC ACID MONOHYDRATE; Sodium Lauroyl Lactylate; ALOE VERA LEAF; SODIUM CITRATE, UNSPECIFIED FORM; Sodium Chloride; Phenoxyethanol; Methylchloroisothiazolinone; Methylisothiazolinone; FD&C BLUE NO. 1; D&C YELLOW NO. 10; EXT. D&C VIOLET NO. 2

CVS Health® MAXIMUM STRENGTH Dandruff Shampoo
Anti-Seborrheic Dermatitis, anti-dandruff

Drug Facts

Active ingredient

Selenium sulfide 1%

Purpose

Anti-Seborrheic Dermatitis, anti-dandruff

Use

for the relief of flaking, and itching associated with dandruff, and seborrheic dermatitis and to help prevent their recurrence.

Warnings

For external use only.

Ask a doctor before using this product if

- condition covers a large area of the body.

When using this product

- avoid contact with the eyes. If contact occurs, rinse eyes thoroughly with water.
- for color-treated or permed hair, rinse thoroughly.

Stop use and ask a doctor if

- condition worsens or does not improve after regular use of this product as directed.

Keep out of reach of children. If swallowed, get medical help or contact a Poison Control Center (1-800-222-1222) right away.

Directions

- shake well
- shampoo, then rinse thoroughly for best results, use at least twice a week or as directed by a doctor.

Other information

- store at room temperature

Inactive ingredients

water, ammonium lauryl sulfate, ammonium laureth sulfate, distearyl phthalic acid amide, cocamide MEA, fragrance, titanium dioxide, dimethicone, hydroxypropyl methylcellulose, citric acid, sodium lauroyl lactylate, aloe barbadensis leaf juice, sodium citrate, sodium chloride, phenoxyethanol, methylchloroisothiazolinone, methylisothiazolinone, blue 1, yellow 10, ext. violet 2.

Questions or comments?

1-866-567-8600

Distributed by: CVS Pharmacy, Inc.
One CVS Drive, Woonsocket, RI 02895

PRINCIPAL DISPLAY PANEL - 325 mL Bottle Label

CVS
Health®

Compare to the active
ingredient in Selsun
Blue® Moisturizing
Dandruff Shampoo*

MAXIMUM STRENGTH

Dandruff
Shampoo

SELENIUM SULFIDE 1%

- For the relief of seborrheic
  dermatitis & dandruff symptoms
- Helps control flakes & itching
- For healthier-looking hair & scalp

MOISTURIZING
+ ALOE

• PARABEN
PHTHALATE •
FREE

11 FL OZ (325 mL)

05-4270